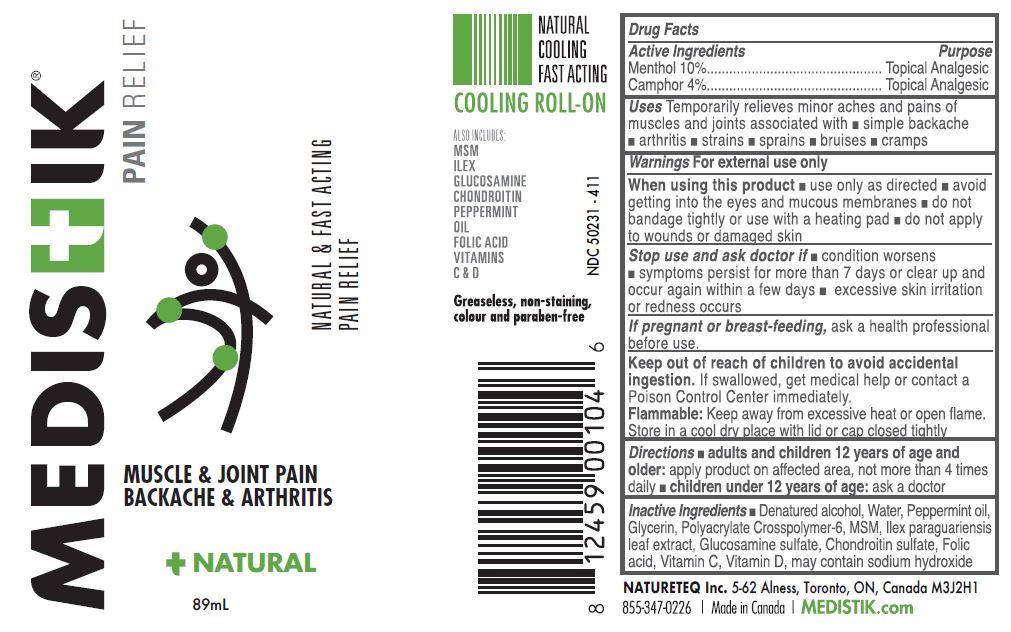 DRUG LABEL: MEDISTIK ICE
NDC: 50231-411 | Form: SOLUTION
Manufacturer: Natureteq Inc.
Category: otc | Type: HUMAN OTC DRUG LABEL
Date: 20250915

ACTIVE INGREDIENTS: MENTHOL 10 g/100 mL; CAMPHOR OIL 4 g/100 mL
INACTIVE INGREDIENTS: ALCOHOL; WATER; PEPPERMINT OIL; GLYCERIN; CARBOMER COPOLYMER TYPE A (ALLYL PENTAERYTHRITOL CROSSLINKED); DIMETHYL SULFONE; ILEX PARAGUARIENSIS LEAF; GLUCOSAMINE SULFATE; CHONDROITIN SULFATE (CHICKEN); FOLIC ACID; ASCORBIC ACID; VITAMIN D

Natureteq (as PLD) - MEDISTIK PRO ICE THERAPY (50231-411)

ACTIVE INGREDIENTS

Menthol 10%

Camphor 4%

PURPOSE

Topical Analgesic

USES

For the temporary relief of sore muscles and joints associated with

- strains and sprains
- backaches
- lumbago
- pain of tendons and/or ligaments
- arthritic or rheumatic pain

WARNINGS

For external use only. Avoid contact with eyes and mucous membranes. Do not apply to wounds or damaged skin. Do not tightly bandage. Do not apply with external heat, such as an electric heating pad, as this may result in excessive skin irritation or skin burn.

Stop use and consult a physician if condition worsens, rash or irritation develops, or if symptoms persist for more than 7 days or clear up and recur in a few days. Consult a health care practitioner prior to use if you are pregnant or breastfeeding. Rashes and/or burning discomfort, and hypersensitivity such as allergy have been known to occur; in which case, discontinue use.

DIRECTIONS

For use on adults and children over 12 years of age.

Apply to affected area(s) 3 to 4 times per day as required. A stinging or burning sensation will be experienced during the first few minutes as the formula begins working. For arthritis or muscle pain of the hands, retain for at least 10 minutes then wash hands.

INACTIVE INGREDIENTS

Denatured alcohol, Water, Peppermint oil, Glycerin, Acrylates copolymer, MSM, Ilex paraguariensis leaf extract, Glucosamine sulphate, Chondroitin sulphate, Folic acid, Vitamin C, Vitamin D.

KEEP OUT OF REACH OF CHILDREN

Cautions: Keep out of reach of children. If overdose or accidental ingestion occurs, call a Poison Control Center immediately.